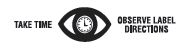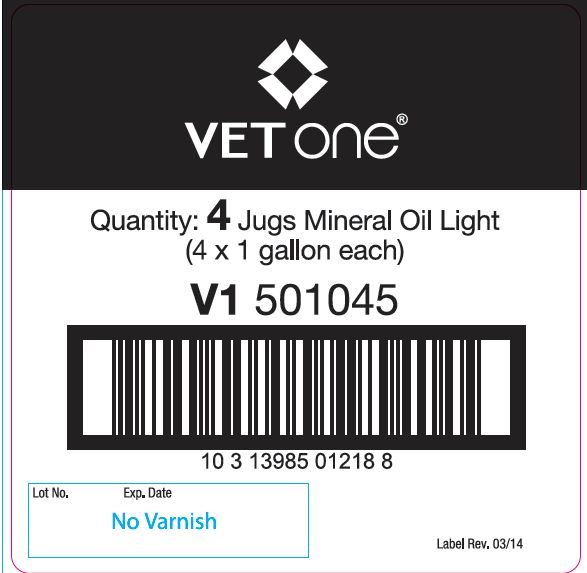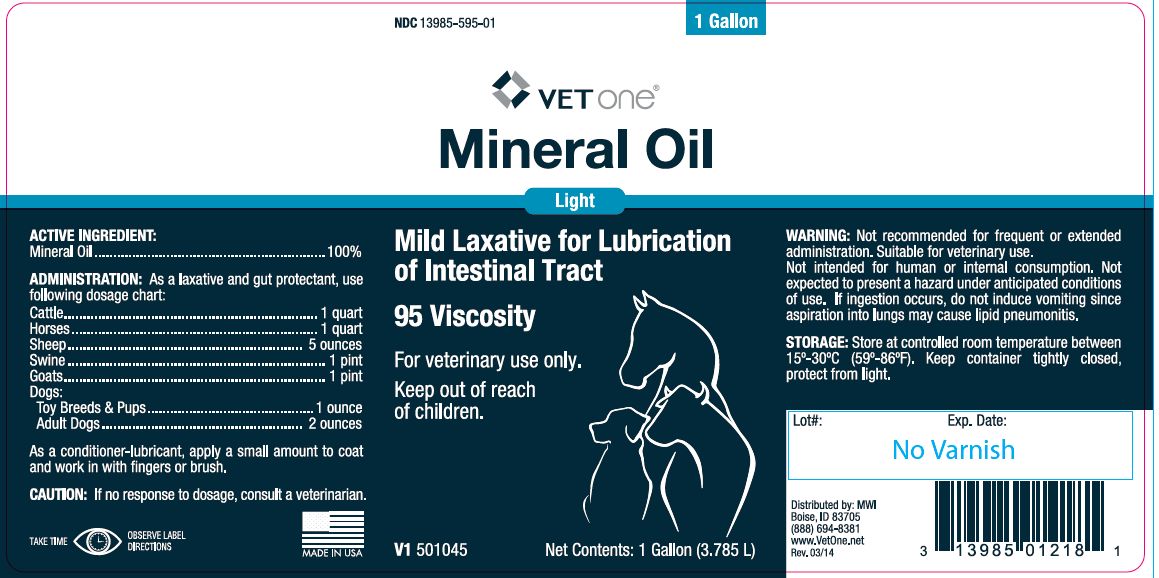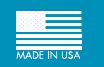 DRUG LABEL: Mineral Oil
NDC: 13985-595 | Form: LIQUID
Manufacturer: MWI/Vet One
Category: animal | Type: OTC ANIMAL DRUG LABEL
Date: 20260219

ACTIVE INGREDIENTS: MINERAL OIL 854.5 g/1 L

Mineral Oil

PURPOSE

Light

Mild Laxative for Lubrication of Intestinal Tract

95 Viscosity

KEEP OUT OF REACH OF CHILDREN

For veterinary use only.

Keep out of reach of children.

ACTIVE INGREDIENT:

Mineral Oil ....................................... 100%

ADMINSTRATION:

As a laxative and gut protectant, use following dosage chart:

Cattle .......................................1 quart

Horses ......................................1 quart

Sheep.....................................5 ounces

Swine......................................... 1 pint

Goats......................................... 1 pint

Dogs:

Toy Breeds & Pups ................1 ounce

Adult Dogs............................2 ounces

As a conditioner-lubricant, apply a small amount to coat and work in with fingers or brush.

CAUTION:

If no response to dosage, consult a veterinarian.

WARNING:

Not recommended for frequent or extended administration. Suitable for veterinary use.

Not intended for human or internal consumption. Not expected to present a hazard under anticipated conditions of use. If ingestion occurs, do not induce vomiting since aspiration into lungs may cause lipid pneumonitis.

STORAGE:

Store at controlled room temperature between 15º-30ºC (59º-86ºF). Keep container tightly closed, protect from light.

Net Contents:

One Gallon (3.785 L) V1 501045

INFORMATION FOR OWNERS/CAREGIVERS

Distributed by: MWI
Boise, ID 83705
(888) 694-8381
www.VetOne.net
Rev. 03/14